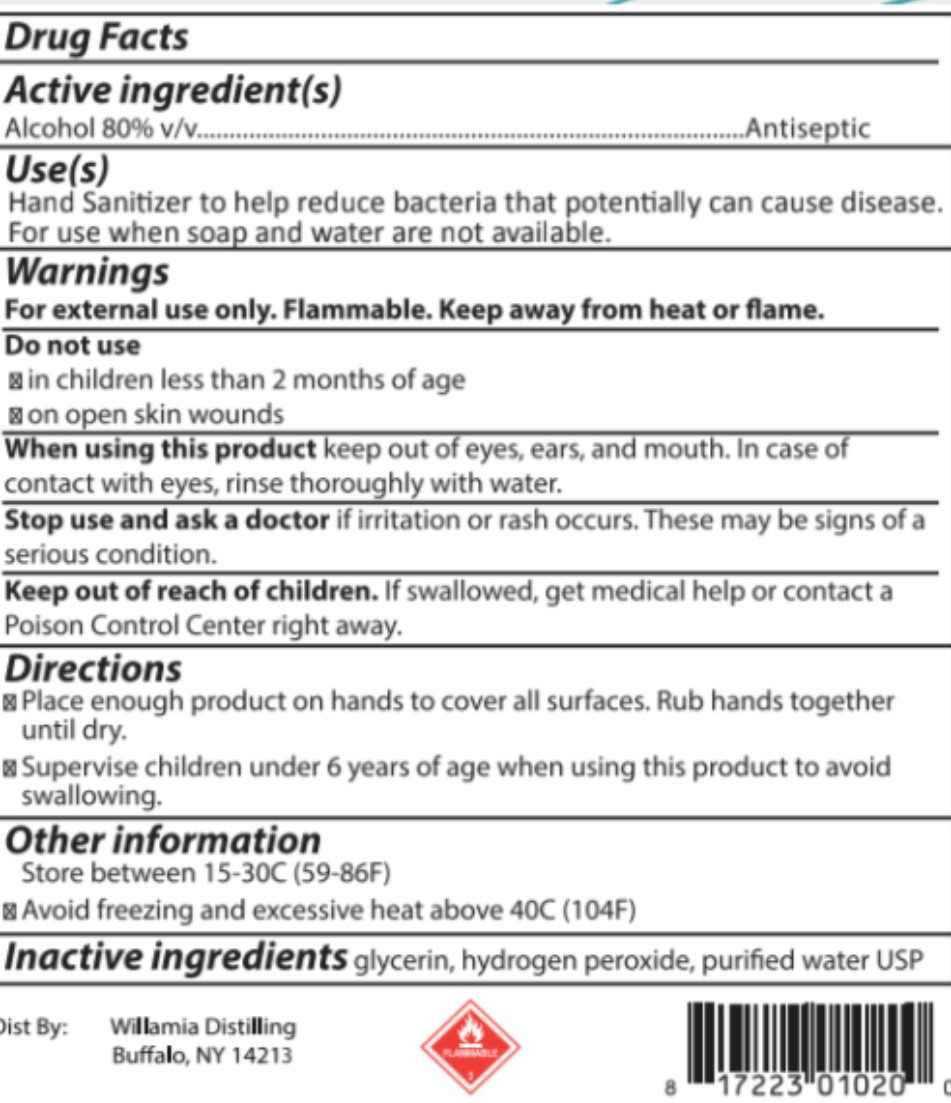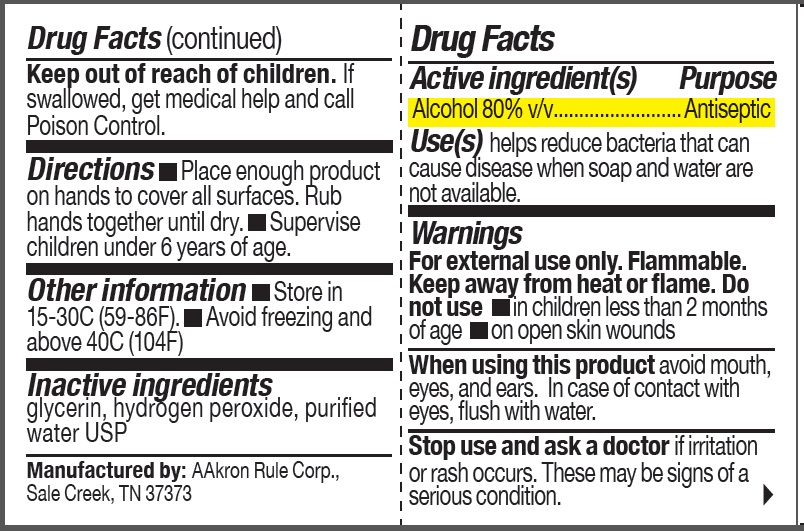 DRUG LABEL: Hand Sanitizer
NDC: 69394-001 | Form: LIQUID
Manufacturer: AAkron Rule Corporation
Category: otc | Type: HUMAN OTC DRUG LABEL
Date: 20220725

ACTIVE INGREDIENTS: ALCOHOL 80 mL/100 mL
INACTIVE INGREDIENTS: GLYCERIN; HYDROGEN PEROXIDE; WATER

Active Ingredient

Alcohol 80% v/v.

Purpose

Antiseptic

Use(S)

helps reduce bacteria that can cause disease when soap and water are not available.

Warnings

For external use only. Flammable. Keep away from heat or flame.

Do not use

- in children less than 2 months of age
- on open skin wounds

When using this product avoid mouth, eyes, and ears. In case of contact with eyes, flush with water .

Stop use and ask a doctor if irritation or rash occurs. These may be signs of a serious condition.

Keep out of reach of children. If swallowed, get medical help and call Poison Control.

Directions

- Place enough product on hands to cover all surfaces. Rub hands together until dry.
- Supervise children under 6 years of age.

Other information

- Store between 15-30C (59-86F)
- Avoid freezing and excessive heat above 40C (104F)

Inactive ingredients

Glycerin, hydrogen peroxide, purified water USP